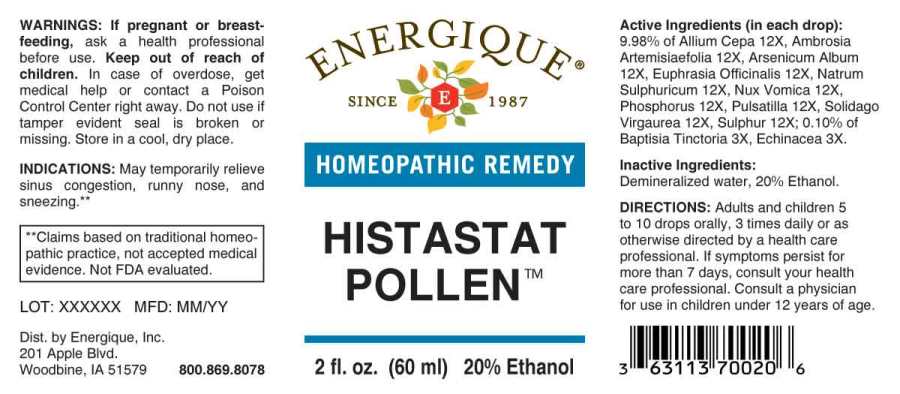 DRUG LABEL: Histastat Pollen
NDC: 44911-0576 | Form: LIQUID
Manufacturer: Energique, Inc.
Category: homeopathic | Type: HUMAN OTC DRUG LABEL
Date: 20241025

ACTIVE INGREDIENTS: BAPTISIA TINCTORIA ROOT 3 [hp_X]/1 mL; ECHINACEA ANGUSTIFOLIA 3 [hp_X]/1 mL; ONION 12 [hp_X]/1 mL; AMBROSIA ARTEMISIIFOLIA 12 [hp_X]/1 mL; ARSENIC TRIOXIDE 12 [hp_X]/1 mL; EUPHRASIA STRICTA 12 [hp_X]/1 mL; SODIUM SULFATE 12 [hp_X]/1 mL; STRYCHNOS NUX-VOMICA SEED 12 [hp_X]/1 mL; PHOSPHORUS 12 [hp_X]/1 mL; ANEMONE PRATENSIS 12 [hp_X]/1 mL; SOLIDAGO VIRGAUREA FLOWERING TOP 12 [hp_X]/1 mL; SULFUR 12 [hp_X]/1 mL
INACTIVE INGREDIENTS: WATER; ALCOHOL

Drug Facts

ACTIVE INGREDIENTS:

(in each drop): 9.98% of Allium Cepa 12X, Ambrosia Artemisiaefolia 12X, Arsenicum Album 12X, Euphrasia Officinalis 12X, Natrum Sulphuricum 12X, Phosphorus 12X, Pulsatilla (Pratensis) 12X, Solidago Virgaurea 12X, Sulphur 12X;0.10% of Baptisia Tinctoria 3X, Echinacea (Angustifolia) 3X.

INDICATIONS:

May temporarily relieve sinus congestion due to hay fever and allergic rhinitis.**

**Claims based on traditional homeopathic practice, not accepted medical evidence. Not FDA evaluated.

WARNINGS:

If pregnant or breast-feeding, ask a health professional before use.

Keep out of reach of children. In case of overdose, get medical help or contact a Poison Control Center right away.

Do not use if tamper evident seal is broken or missing.

Store in a cool, dry place.

Keep out of reach of children. In case of overdose, get medical help or contact a Poison Control Center right away.

DIRECTIONS:

Adults and children 5 to 10 drops orally, 3 times daily or as otherwise directed by a health care professional. If symptoms persist for more than 7 days, consult your health care professional. Consult a physician for use in children under 12 years of age.

INDICATIONS:

May temporarily relieve sinus congestion due to hay fever and allergic rhinitis.**

**Claims based on traditional homeopathic practice, not accepted medical evidence. Not FDA evaluated.

INACTIVE INGREDIENTS:

Demineralized water, 20% Ethanol.

QUESTIONS:

Dist. by Energique, Inc.

201 Apple Blvd.

Woodbine, IA 51579

800-869-8078

PACKAGE LABEL DISPLAY:

ENERGIQUE

SINCE 1987

HOMEOPATHIC REMEDY

HISTASTAT POLLEN

2 fl. oz. (60 ml)